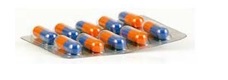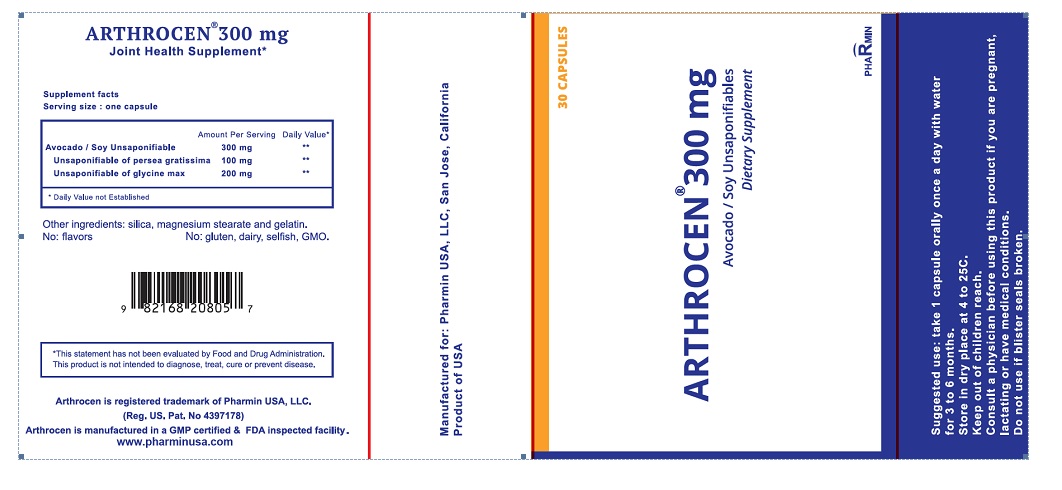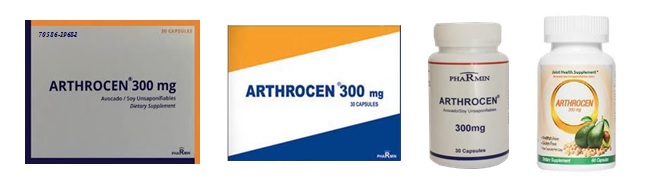 DRUG LABEL: ARTHROCEN 300 mg
NDC: 70586-2012 | Form: CAPSULE
Manufacturer: Pharmin USA, LLC
Category: other | Type: DIETARY SUPPLEMENT
Date: 20170829

ACTIVE INGREDIENTS: AVOCADO OIL UNSAPONIFIABLES 100 mg/1 1; SOYBEAN 200 mg/1 1
INACTIVE INGREDIENTS: MAGNESIUM STEARATE; GELATIN, UNSPECIFIED; FD&C YELLOW NO. 5; TITANIUM DIOXIDE; TOCOPHEROL; SOY PROTEIN; SILICON DIOXIDE; MICROCRYSTALLINE CELLULOSE; ACACIA; WATER

ARTHROCEN 300 mg

ARTHROCEN 300 MG- Avocado/Soy Unsaponifiables (ASU) Pharmin USA, LLC HIGHLIGHTS OF PRESCRIBING INFORMATION DIETARY SUPPLEMENT Arthrocen is classified as a dietary supplement in the US, however, in some other countries it is categorized as a prescription drug.

1 INDICATION AND USAGE

Rheumatology: Arthrocen 300 mg Capsules is indicated to treat connective tissues in osteoarthritis and prevent cartilage degradations.

Dentistry: Arthrocen Capsules is indicated to treat periodontitis.

2 DOSAGE AND ADMINISTATION

The recommended dose of Arthrocen Capsules for adult is one capsule a day preferably with a meal. It may take up to 3 to 6 months for desired effects.

3 DOSAGE FORMS AND STRENGHTS

Capsules: 300 mg avocado/soy unsaponifiables per capsule.

4 CONTRAINDICATIONS

History of hypersensitivity to soy or any of the product components.

5 WARNINGS AND PRECAUTIONS

This product has been prescribed for a particular condition, therefore, this medicine should not be used for other conditions. Do not give this medicine to anyone else. Keep this and all medicines out of the reach of children. This medicine should not be used after the expiration date. This product is presented in capsules made of hard gelatin.

6 ADVERSE REACTIONS

Infrequent: in some patients, it may cause stomach upset. To avoid this discomfort capsules should be taken with meals.

Rare: hypersensitivity to soy or any of the product components.

7 Preclinical and Clinical Trail Experience

Chondroprotective, anabolic, and anticatabolic effects of Avocado/Soy Unsaponifiables have been demonstrated in several studies of Avocado/Soy Unsaponifiables solid dosage form.

A- Human Clinical Studies
The efficacy and safety of Arthrocen, avocado/soybean unsaponifiables, with that of placebo assessed in treatment of patients with knee osteoarthritis (OA). Research indicated a significant difference was demonstrated between the daily dose of Arthrocen 300 mg and placebo after 9 months of follow-up, patients treated with Arthrcoen 300 mg were significantly improved compared to placebo in terms of LI (<0.001) and VAS (P < 0.01). Daily amount of analgesics reduced significantly from baseline 67% to 12.2% at the final visit. This study suggests that a daily administration of 300 mg oral Arthrocen allows a significant clinical improvement compared to placebo after 6 months relieving joint stiffness, pain as well as enhancing ability to conduct daily functions with reduction in analgesics' intakes.

Further four double-blind placebo-controlled randomized trials (Appelboom et al.; Blotman et al.; Lequesne et al.; Maheu et al.), a meta-analysis (Christensen et al.), and two systematic reviews (Ameye and Chee ; Ernst) evaluated the effects of ASUs on knee and hip OA. As for safety, none of the four trials reported adverse effects of ASU when 300 - 600mg ASU/day was administered for 3 months to 2 years (mean age of subjects 62-65 y).

B- Animal Study
Goudarzi et al showed Arthrocen can reduce joint pain in OA animal model. OA was induced in male Wistar rats by intra-articular injection of sodium monoiodoacetate (MIA: 0.3mg) and animals were allowed to recover for 14 days. Arthrocen was added to the drinking water which was available to animals ad libitum. On day 30, joint pain was assessed by dynamic incapacitance while referred pain was determined by von Frey hair algesiometry.

The joint damage induced by MIA injection was severe and was consistent with end-stage OA. Arthrocen consumption (approximately 35 mg/day) attenuated the joint oedema associated with MIA injection. Hindlimb weight bearing also significantly improved in Arthrocen-treated rats (P<0.05); however, von Frey hair mechanosensitivity was unaffected by this treatment. These data indicate that Arthrocen has the potential to reduce joint inflammation and pain associated with end-stage OA. No adverse effects were noted.

Preclinical Trail Experience
A-Goudarzi et al found a role for Arthrocen in attenuating the inflammatory response both at the protein and mRNA level. Furthermore, Arthrocen diminished prostaglandin E2 (PGE2) levelsin response to an inflammatory trigger. Unlike traditional COX-2 inhibitors, this response rather specifically attenuated PGE2 levels in the presence of inflammation and without lowering levels of other eicosanoids. This implies that Arthrocen could potentially bring about the reduced pain produced by COX-2 inhibitors without the known side effects of COX-2 inhibition.

B- Taylor et al found a role for Arthrocen in attenuating the inflammatory response at the mRNA level while inducing significant changes in numerous cytokines. They discovered that while Arthrocen alone did not increase IL-8 or MCP1 levels, its presence had a synergistic effect on the observed increase in response to LPS stimulation. Additionally, this synergistic effect of Arthrocen on LPS stimulation of IL-8 and MCP1 protein levels was also observed at the mRNA level and suggests a regulatory mechanism at the transcriptional level. Interestingly, Arthrocen induced no changes in any of the eicosanoids studied. This multi-omics approach implies that Arthrocen functions at the level of gene transcription to attenuate inflammation mediated by monocytes in OA.

8 Post Marketing Experience

Since side effects are reported voluntarily from a population of uncertain size, it is not always possible to estimate their frequency or to establish a causal relationship to drug exposure. The following adverse effect identified during post-approval of avocado soy usaponifiables: nausea and stomach upset

9 DRUG INTERACTION:

Severe interactions were not reported. Nevertheless, to avoid interactions with other drugs, the patient shall inform the physician if she/he is taking another medicine.

10 USE IN SPECIFIC POPULATION

10.1 Pregnancy

There is not available data to evaluate teratogenic or fetotoxic effects, therefore, it should not be used during pregnancy and breastfeeding. Therefore, not recommended during pregnancy.

10.2 Labor and Delivery

The effects of avocado soy Unsaponifiables on labor and delivery are unknown.

Therefore, not recommended during labor.

10.3 Nursing Mothers

The effects of avocado soy Unsaponifiables on nursing mother are unknown.

Therefore, not recommended during lactation.

OVERDOSAGE

11 OVER DOSAGE: None reported.

12 Effects on ability to drive and use machines: None reported.

13. DESCRIPTION

Arthrocen 300 mg Capsules:

Avocado/Soy Unsaponifiables (A1S2U)

• Unsaponifiable of Avocado 100 mg (1 part)

• Unsaponifiable of Soybean 200 mg (2 parts)

ASU is an anti-osteoarthritic agent that has been derived from the unsaponiﬁable residues of avocado and soybean, and mixed in a ratio of 1:2 respectively. It has been suggested that its phytosterol components are responsible for up-regulation of glycosaminoglycan and collagen synthesis and reduction of pro inflammatory mediators. The synergistic activity between avocado and soybean, and their relative ratios, has been found to be significantly effective.

The major components of ASU by weight are the phytosterols, such as beta-sitosterol, campesterol and stigmasterol. Other components of ASU include fat-soluble vitamins, triterpene alcohols and possibly furan fatty acids.

14. CLINICAL PHARMACOLOGY

ASU possesses chondroprotective, anabolic, and anticatabolic properties. It inhibits the breakdown of cartilage and promotes cartilage repair by inhibiting a number of molecules and pathways implicated in osteoarthritis.

14.1 Mechanism of Action:

ASU stimulates the synthesis of collagen and aggrecan by inhibiting inflammatory cytokines such as IL-1, IL-6, IL-8, TNF, and PGE2 through modulation of NF-kappaB. ASU inhibitory affects an array of inflammatory molecules including expression of COX-2 and production of PGE2 in chondrocytes. COX-2 regulates the production of PGE2; both are mediators involved in the process of cartilage breakdown. ASU also inhibits the release and activity of collagenase (MMP2) and stromelysin 1 (MMP3) in cultured chondrocytes increases tissue inhibitors of metalloproteinases (TIMP- 1) and inhibits IL1-induced ERK in chondrocytes in vitro.

14.2 Pharmacokinetics and Distributions:

Phytosterols are primarily eliminated via feces fast, however, remnants may stay up few days in the organs. The absorptions are slightly higher in women than men and can be measured through biliary eliminations.

Researches indicate phytosterols can be distributed fairly similarly in any organs. The adrenal glands, ovaries and intestinal epithelia showing the maximum retention of phytosterols.

15. NONCLINICAL TOXICOLOGY

15.1 Toxicology

There is no ASU toxicological side effects were reported up at the dose of 300 mg a day.

15.2 Carcinogenesis, Mutagenesis, Impairment Of Fertility
No carcinogenicity, mutagenicity, or fertility studies have been conducted with ASU.

HOW SUPPLIED/STORAGE AND HANDLING

Each Arthrocen Capsule, intended for oral administration, is orange-purple bovine zero size capsule.

Each Arthrocen capsule contains 300 mg avocado soy unsaponifiables and are supplied as follows:

NDC 70586-2012-1 Bottles of 60 capsules.
NDC 70586-2012-5 Boxes of 30 capsules in blisters.

Arthrocen possesses various outer display packaging worldwide:

STORAGE:

Store at 20° to 25°C (68° to 77°F) excursions permitted between 15° to 30°C (59° to 86°F) [See USP Controlled Room Temperature].

LICENSE HOLDER:

Pharmin USA, LLC
Arthrocen is a registered trademark of Pharmin USA, LLC
US Reg. No: 4397178

Manufactured For:

Pharmin USA, LLC
San Jose, California 95128

United States of America

Address inquiries to Pharmin USA, LLC, info@pharminusa.com, www.pharminusa.com.

Arthrocen is manufactured in GMP and FDA inspected facility in State of California.

Made in USA

Package label principal display panel (30 capsules):

NDC: 70586-2012-5
Barcode No: 982168208057

SWALLOW CAPSULES. DO NOT CHEW.

Consult a physician before using this product or any dietary supplement.

Take one capsule per day.
It may take up to 3 to 6 months for desired effects. Keep out of the reach of children.
Shellfish and Gluten free.

Dairy and flavor Free.
One capsule a day.
Non GMO.

Contain: SOY

S U P P L E M E N T F A C T S
Serving Size: 1 Capsule Serving Per Container: 30
 | Amount Serving | % Daily Value
Avocado/Soy Unsaponifiables | 300 mg | *
Avocado Unsaponifiables | 1 part
Soy Unsaponifiables | 2 parts

*Daily value not established

Other ingredients:
Magnesium Stearate, gelatin fines, FD&C #5 colorant, titanium dioxide, mixed tocopherols, soy protein isolate, silicon dioxide, microcrystalline cellulose and acacia gum.